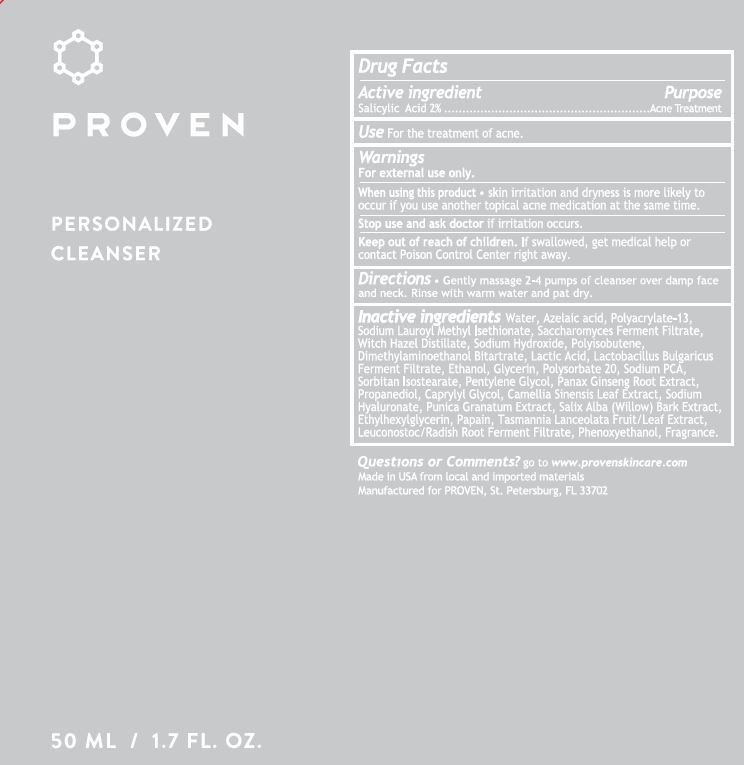 DRUG LABEL: Proven Acne Cleanser
NDC: 73572-011 | Form: CREAM
Manufacturer: Proven Skincare
Category: otc | Type: HUMAN OTC DRUG LABEL
Date: 20240101

ACTIVE INGREDIENTS: SALICYLIC ACID 2 g/100 g
INACTIVE INGREDIENTS: AZELAIC ACID; DEANOL BITARTRATE; LACTOBACILLUS DELBRUECKII BULGARICUS; PROPANEDIOL; SODIUM HYDROXIDE; WITCH HAZEL; SORBITAN ISOSTEARATE; WATER; ALCOHOL; ETHYLHEXYLGLYCERIN; FRAGRANCE 13576; POLYACRYLATE-13; SODIUM PCA; CAMELLIA SINENSIS LEAF; EDETATE DISODIUM; PAPAIN; PENTYLENE GLYCOL; PHENOXYETHANOL; POLYISOBUTYLENE (55000 MW); PUNICA GRANATUM ROOT BARK; LEUCONOSTOC/RADISH ROOT FERMENT FILTRATE; PANAX GINSENG ROOT; POLYSORBATE 20; SALIX ALBA BARK; SODIUM LAUROYL ISETHIONATE; CAPRYLYL GLYCOL; GLYCERIN; LACTIC ACID; SACCHAROMYCES CEREVISIAE; TASMANNIA LANCEOLATA FRUIT; XANTHAN GUM; SODIUM CHLORIDE; SODIUM HYALURONATE

Proven Personalized Cleanser

ACTIVE INGREDIENT

Salicylic Acid 2%

PURPOSE

Acne Treatment

INDICATIONS AND USAGE

Use For the treatment of acne.

Warnings

For external use only.

When using this product - skin irritation and dryness is more likely to occur if you use another topical acne medication at the same time.

Stop use and ask doctor if irritation occurs.

Keep out of reach of children. If swallowed, get medical help or contact Poison Control Center right away.

Directions

Gently massage 2-4 pumps of cleanser over damp face and neck. Rinse with warm water and pat dry.

INACTIVE INGREDIENT

Azelaic acid

Camellia Sinensis Leaf Extract

Caprylyl Glycol

Dissodium EDTA

DMAE Bitartrate

Ethanol

Ethylhexylglycerin

Fragrance

Glycerin

Lactic Acid

Lactobacillus Bulgaricus Ferment Filtrate

Leuconostoc/Radish Root Ferment Filtrate

Panax Ginseng Root Extract

Papain

Pentylene Glycol

Phenoxyethanol

Polyacrylate-13

Polyisobutene

Polysorbate 20

Propanediol

Punica Granatum Extract

Saccharomyces Ferment

Salix Alba (Willow) Bark Extract

Sodium Chloride

Sodium Hyaluronate

Sodium PCA

Sodium Hydroxide

Sodium Lauroyl Isethionate

Sorbitan Isostearate

Tasmannia Lanceolata Fruit/Leaf Extract

Water

Witch Hazel Distillate

Xanthum Gum

QUESTIONS

Go to www.provenskincare.com